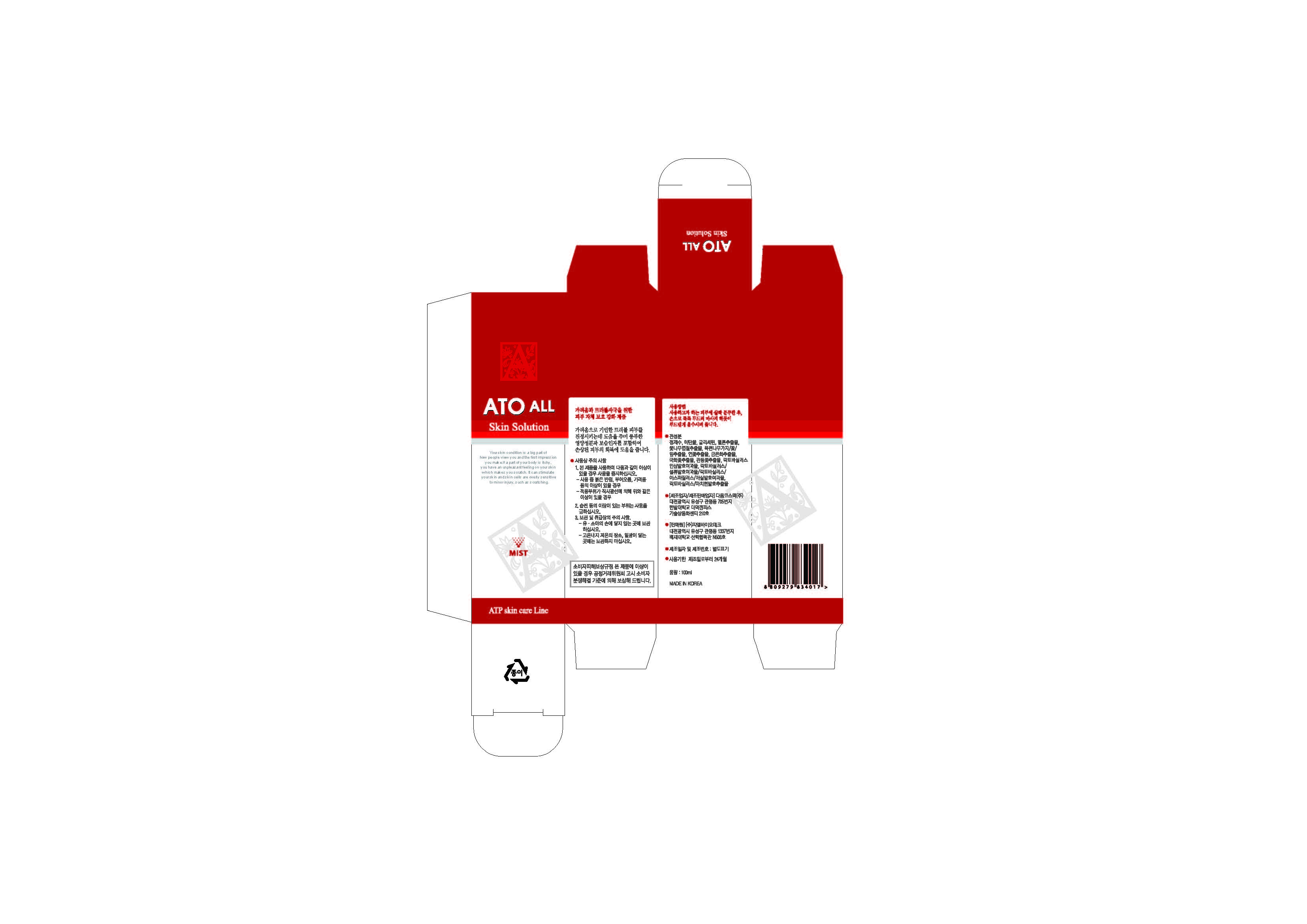 DRUG LABEL: ATO ALL
NDC: 69224-1001 | Form: LIQUID
Manufacturer: GL BioTech 
Category: otc | Type: HUMAN OTC DRUG LABEL
Date: 20141017

ACTIVE INGREDIENTS: GLYCERIN 2 g/100 mL
INACTIVE INGREDIENTS: WATER; ALCOHOL

Drug Facts

ACTIVE INGREDIENT

glycerin

INACTIVE INGREDIENT

melon ext, lactobacillus, fermented ginseng ext, pomegranate ext, plum ext, lotus flower ext, etc

PURPOSE

for itching skin, lichenous skin trouble, skin balancing

keep out or reach of the children

INDICATIONS AND USAGE

1. For the first 5 days, spray 3 times a day for
breakfast, lunch and dinner
2. After shower dry your body completely and
then spray.
3. Spraying on the trouble spot may hurt due to
disinfecting action.
4. Please refrain from the food that
accompanies a skin reaction.
5. After use, you might want to use the other
basic cosmetic products.

WARNINGS

- avoid direct sun exposure, keep it refrigerated or in cooler places
- do not eat

DOSAGE AND ADMINISTRATION

for exernal use only